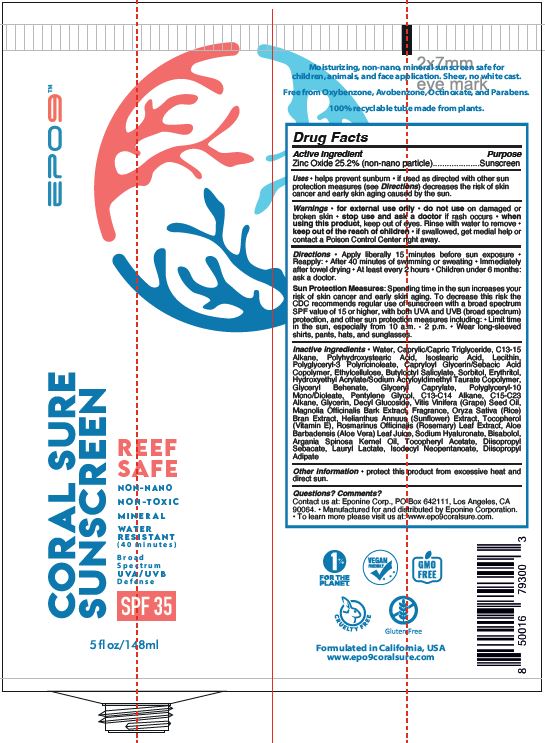 DRUG LABEL: CORAL SURE SUNSCREEN
NDC: 79811-101 | Form: LOTION
Manufacturer: EPONINE LABS LLC
Category: otc | Type: HUMAN OTC DRUG LABEL
Date: 20220710

ACTIVE INGREDIENTS: ZINC OXIDE 25.2 g/100 mL
INACTIVE INGREDIENTS: HELIANTHUS ANNUUS WHOLE; ALOE VERA LEAF; HYALURONATE SODIUM; .ALPHA.-BISABOLOL, (+)-; LAURYL LACTATE; ISODECYL NEOPENTANOATE; DECYL GLUCOSIDE; ARGAN OIL; GLYCERIN; GRAPE SEED OIL; MAGNOLIA OFFICINALIS BARK; RICE BRAN; C15-23 ALKANE; .BETA.-TOCOPHEROL; ROSEMARY; ALPHA-TOCOPHEROL ACETATE; DIISOPROPYL SEBACATE; WATER; MEDIUM-CHAIN TRIGLYCERIDES; C13-15 ALKANE; LECITHIN, SUNFLOWER; POLYGLYCERYL-3 RICINOLEATE; CAPRYLOYL GLYCERIN/SEBACIC ACID COPOLYMER (2000 MPA.S); ETHYLCELLULOSE (10 MPA.S); ISOSTEARIC ACID; POLYHYDROXYSTEARIC ACID (2300 MW); BUTYLOCTYL SALICYLATE; SORBITOL; ERYTHRITOL; HYDROXYETHYL ACRYLATE/SODIUM ACRYLOYLDIMETHYL TAURATE COPOLYMER (45000 MPA.S AT 1%); GLYCERETH-2 COCOATE; GLYCERYL CAPRYLATE; POLYGLYCERYL-10 DIOLEATE; PENTYLENE GLYCOL; DIISOPROPYL ADIPATE

EPO9 - CORAL SURE SUNSCREEN SPF35 (79811-101)

ACTIVE INGREDIENTS

Zinc Oxide 25.2%

PURPOSE

SUNSCREEN

USES

• helps prevent sunburn.
• if used as directed with other sun protection measures (see Directions), decreases the risk of skin cancer and early skin aging caused by the sun.

WARNINGS

- for external use only
- do not use on damaged or broken skin
- stop use and ask a doctor if rash occurs
- when using this product, keep out of eyes. Rinse with water to remove

Keep out of reach of children. If swallowed, get medical help or contact a Poison Control Center right away.

DIRECTIONS

• Apply liberally 15 minutes before sun exposure • Reapply: • After 40 minutes of swimming or sweating • Immediately
after towel drying • At least every 2 hours • Children under 6 months: ask a doctor.

Sun Protection Measures: Spending time in the sun increases your risk of skin cancer and early skin aging. To decrease this risk the CDC recommends regular use of sunscreen with a broad spectrum SPF value of 15 or higher, with both UVA and UVB (broad spectrum) protection, and other sun protection measures including: • Limit time in the sun, especially from 10 a.m. - 2 p.m. • Wear long-sleeved shirts, pants, hats, and sunglasses.

INACTIVE INGREDIENT

Water, Caprylic/Capric Triglyceride, C13-15 Alkane, Polyhydroxystearic Acid, Isostearic Acid, Lecithin, Polyglyceryl-3 olyricinoleate, Capryloyl Glycerin/Sebacic Acid Copolymer, Ethylcellulose, Butyloctyl Salicylate, Sorbitol, Erythritol, Hydroxyethyl Acrylate/Sodium Acryloyldimethyl Taurate Copolymer, Glyceryl Behenate, Glyceryl Caprylate, Polyglyceryl-10 Mono/Dioleate, Pentylene Glycol, C13-C14 Alkane, C15-C23 Alkane, Glycerin, Decyl Glucoside, Vitis Vinifera (Grape) Seed Oil, Magnolia Officinalis Bark Extract, Fragrance, Oryza Sativa (Rice) Bran Extract, Helianthus Annuus (Sunflower) Extract, Tocopherol (Vitamin E), Rosmarinus Officinalis (Rosemary) Leaf Extract, Aloe Barbadensis (Aloe Vera) Leaf Juice, Sodium Hyaluronate, Bisabolol, Argania Spinosa Kernel Oil, Tocopheryl Acetate, Diisopropyl Sebacate, Lauryl Lactate, Isodecyl Neopentanoate, Diisopropyl Adipate

QUESTIONS? COMMENTS?

Contact us at: Eponine Corp., PO Box 642111, Los Angeles, CA 90064. • Manufactured for and distributed by Eponine Corporation.
• To learn more please visit us at: www.epo9coralsure.com.

OTHER INFORMATION

• protect this product from excessive heat and direct sun.